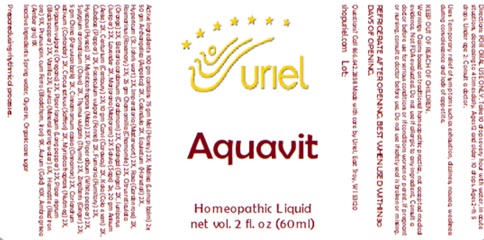 DRUG LABEL: Aquavit
NDC: 48951-1347 | Form: LIQUID
Manufacturer: Uriel Pharmacy Inc.
Category: homeopathic | Type: HUMAN OTC DRUG LABEL
Date: 20250606

ACTIVE INGREDIENTS: CARDAMOM 2 [hp_X]/1 mL; LESSER GALANGAL ROOT 2 [hp_X]/1 mL; JUNIPER BERRY 2 [hp_X]/1 mL; LAVANDULA ANGUSTIFOLIA FLOWER 2 [hp_X]/1 mL; LITSEA CUBEBA FRUIT 2 [hp_X]/1 mL; FUMARIA OFFICINALIS FLOWERING TOP 2 [hp_X]/1 mL; BLACK PEPPER 2 [hp_X]/1 mL; FERRIC OXIDE RED 9 [hp_X]/1 mL; PRUNUS SPINOSA FLOWER BUD 9 [hp_X]/1 mL; HYSSOPUS OFFICINALIS WHOLE 2 [hp_X]/1 mL; SYZYGIUM AROMATICUM FRUIT 2 [hp_X]/1 mL; GINGER 2 [hp_X]/1 mL; IMPERATORIA OSTRUTHIA ROOT 2 [hp_X]/1 mL; OREGANO 2 [hp_X]/1 mL; SEDUM ROSEUM WHOLE 2 [hp_X]/1 mL; VANILLA BEAN 2 [hp_X]/1 mL; MYRISTICA FRAGRANS WHOLE 2 [hp_X]/1 mL; QUILLAJA SAPONARIA BARK 2 [hp_X]/1 mL; CINNAMON 2 [hp_X]/1 mL; CORIANDER OIL 2 [hp_X]/1 mL; WHITE PEPPER 2 [hp_X]/1 mL; FERROUS ARSENATE 6 [hp_X]/1 mL; AMBERGRIS 11 [hp_X]/1 mL; ANISE 2 [hp_X]/1 mL; CENTAURIUM ERYTHRAEA FLOWERING TOP 2 [hp_X]/1 mL; ANGELICA ARCHANGELICA ROOT 2 [hp_X]/1 mL; ROSMARINUS OFFICINALIS FLOWERING TOP 2 [hp_X]/1 mL; CALENDULA OFFICINALIS FLOWERING TOP 2 [hp_X]/1 mL; EQUISETUM ARVENSE TOP 2 [hp_X]/1 mL; ST. JOHN'S WORT 2 [hp_X]/1 mL; GOLD 10 [hp_X]/1 mL; HONEY 2 [hp_X]/1 mL; CHAMOMILE 2 [hp_X]/1 mL; TANGERINE 2 [hp_X]/1 mL; FENNEL SEED 2 [hp_X]/1 mL; THYME 2 [hp_X]/1 mL; SAFFRON 2 [hp_X]/1 mL; NUTMEG 2 [hp_X]/1 mL; LONG PEPPER 2 [hp_X]/1 mL; SWEET MARJORAM 2 [hp_X]/1 mL; CARAWAY SEED 2 [hp_X]/1 mL; COLA NITIDA SEED 2 [hp_X]/1 mL
INACTIVE INGREDIENTS: GLYCERIN; SUCROSE; WATER

Aquavit

INDICATIONS AND USAGE

Directions: FOR ORAL USE ONLY.

DOSAGE AND ADMINISTRATION

Take 10 drops every hour with water, in acute situations, decreasing to 4 times daily. Ages 12 and older: 10 drops. Ages 2-11: 5 drops. Under age 2: Consult a doctor.

ACTIVE INGREDIENT

Active Ingredients: 100 gm contains: 75 gm Mel (Honey) 2X; Melissa (Lemon balm) 2X, 50 gm Archangelica (Angelica) 2X, Calendula 2X, Equisetum (Horsetail) 2X, Hypericum (St. John's wort) 2X, Imperatoria (Masterwort) 2X, Rosa (Garden rose) 2X, Rosmarinus (Rosemary) 2X; 25 gm Chamomilla (Chamomile) 2X, Citrus reticulata (Orange) 2X, Elettaria cardamum (Cardamom) 2X, Galangal (Ginger) 2X, Juniperus (Juniper) 2X, Lavender 2X, Marjorana (Marjoram) 2X; Salvia (Sage) 2X, 20 gm Anisum (Anise) 2X, Centurium (Centaury) 2X; 10 gm Carvi (Caraway) 2X, Kola (Cola e sem) 2X, Cubebae (Pepper) 2X, Foeniculum vulgare (Fennel) 2X, Fumaria (Fumitory) 2X, Hyssopus (Hyssop) 2X, Myristica fragrans (Mace) 2X, Piper album (White pepper) 2X, Syzygium aromaticum (Clove) 2X, Thymus vulgaris (Thyme) 2X, Zingiberis (Ginger) 2X; 5 gm China (Peruvian bark) 2X, Cinnamomum cassia (Cinnamon) 2X, Coriandrum sativum (Coriander) 2X, Crocus sativus (Saffron) 2X, Myristica fragrans (Nutmeg) 2X, Origanum vulgare (Oregano) 2X, Piper longum (Long pepper) 2X, Piper nigrum (Black pepper) 2X, Vanilla 2X; Levico (Mineral spring water) 6X, Hematite (Red iron ore) 9X, Prunus spin. cum Ferro (Blackthorn, Iron) 9X, Aurum (Gold) 10X, Ambra grisea (Amber gris) 11x

Inactive Ingredients: Spring water, Glycerin, Organic cane sugar

Prepared using rhythmical processes

PURPOSE

Uses: Temporary relief of symptoms such as exhaustion, dizziness, nausea, weakness during convalescence and lack of appetite.

KEEP OUT OF REACH OF CHILDREN.

WARNINGS

Warnings: Claims based on traditional homeopathic practice, not accepted medical evidence. Not FDA evaluated. Do not use if allergic to any ingredient. Consult a doctor before use for serious conditions or if conditions worsen or persist. If pregnant or nursing, consult a doctor before use. Do not use if safety seal is broken or missing.

Refrigerate after opening. Best when used within 30days of opening.

Questions? Call 866.642.2858
Made with care by Uriel, East Troy, WI 53120
shopuriel.com Lot#